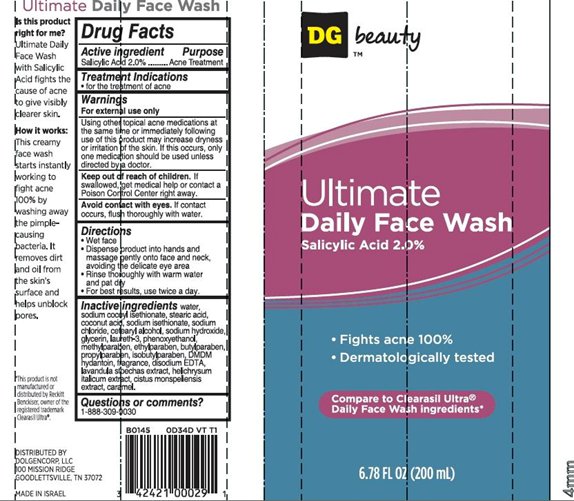 DRUG LABEL: Ultimate Daily Face Wash
NDC: 55910-333 | Form: CREAM
Manufacturer: Dolgencorp Inc.
Category: otc | Type: HUMAN OTC DRUG LABEL
Date: 20140110

ACTIVE INGREDIENTS: SALICYLIC ACID 2 g/100 mL
INACTIVE INGREDIENTS: WATER; SODIUM COCOYL ISETHIONATE; CETOSTEARYL ALCOHOL; STEARIC ACID; SODIUM HYDROXIDE; GLYCERIN; LAURETH-3; PHENOXYETHANOL; METHYLPARABEN; ETHYLPARABEN; BUTYLPARABEN; PROPYLPARABEN; ISOBUTYLPARABEN; DMDM HYDANTOIN; CARAMEL; EDETATE DISODIUM; LAVANDULA STOECHAS FLOWERING TOP; HELICHRYSUM ITALICUM FLOWER; CISTUS MONSPELIENSIS LEAF

DG™ beauty Ultimate Daily Face Wash

Active ingredient

Salicylic Acid 2.0%

Purpose

Acne Treatment

Treatment Indications

- for the treatment of acne

Warnings

For external use only.

Using other topical acne medications at the same time or immediately following use of this product may increase dryness or irritation of the skin. If this occurs, only one medication should be used unless directed by a doctor.

Keep Out of Reach of Children.

If swallowed, get medical help or contact a Poison Control Center right away.

Avoid contact with eyes.

If contact occurs, flush thoroughly with water.

Directions

- Wet face
- Dispense product into hands and massage gently onto face and neck, avoiding the delicate eye area
- Rinse thoroughly with warm water and pat dry
- For best results, use twice daily

Inactive Ingredients

water, sodium cocoyl isethionate, stearic acid, coconut acid, sodium isethionate, sodium chloride, cetearyl alcohol, sodium hydroxide, glycerin, laureth-3, phenoxyethanol, methylparaben, ethylparaben, butylparaben, propylparaben, isobutylparaben, DMDM hydantoin, fragrance, disodium EDTA, lavandula stoechas extract, helichrysum italicum extract, cistus monspeliensis extract, caramel.

Questions or comments?

1-888-309-9030

Package/Label Principal Display Panel

DG™ beauty Ultimate Daily Face Wash
Salicylic Acid 2.0%

- Fight acne 100%
- Dermatologically tested

Compare to Clearasil Ultra®
Daily Face Wash Ingredients*

6.78 FL OZ (200 mL)

*This product is not manufactured or distributed by Reckitt Bencloser, owner of the registered trademark Clearasil Ultra®

DISTRIBUTED BY:
DOLGENCORP, LLC
100 MISSION RIDGE
GOODLETTSVILLE, TN 37072
MADE IN ISRAEL

Carton Label